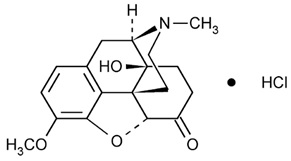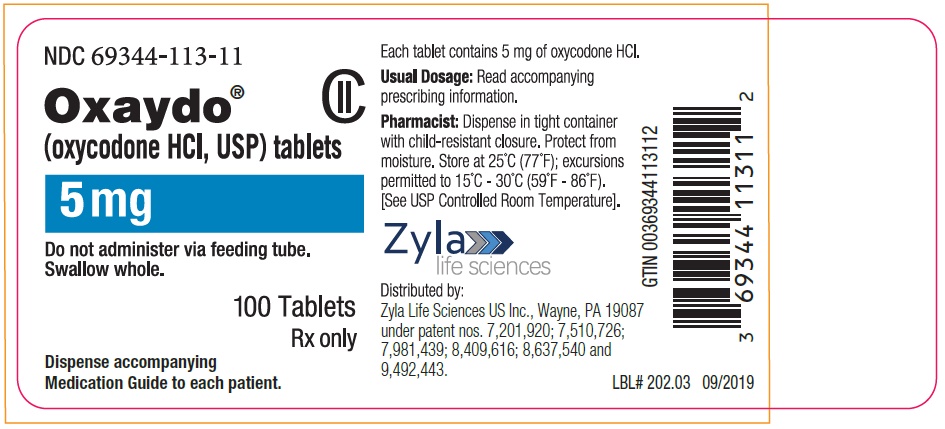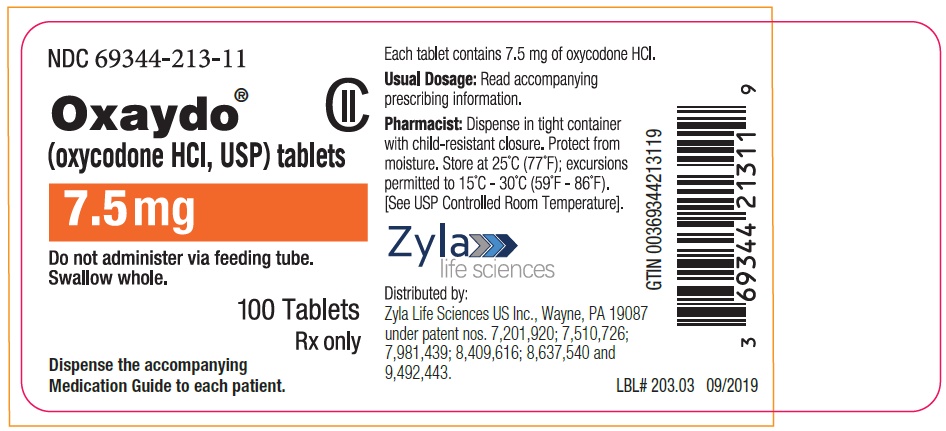 DRUG LABEL: OXAYDO
NDC: 69344-113 | Form: TABLET
Manufacturer: Zyla Life Sciences US LLC
Category: prescription | Type: HUMAN PRESCRIPTION DRUG LABEL
Date: 20260104
DEA Schedule: CII

ACTIVE INGREDIENTS: OXYCODONE HYDROCHLORIDE 5 mg/1 1

HIGHLIGHTS OF PRESCRIBING INFORMATION

These highlights do not include all the information needed to use OXAYDO safely and effectively. See full prescribing information for OXAYDO.
OXAYDO® (oxycodone HCl) tablets for oral use only – CII
Initial U.S. Approval: 1950

RECENT MAJOR CHANGES

Boxed Warning 12/2025

Indications and Usage (1) 12/2025

Dosage and Administration (2.2, 2.5) 12/2025

Warnings and Precautions (5.1, 5.2, 5.3, 5.12, 5.14) 12/2025

WARNING: SERIOUS AND LIFE-THREATENING RISKS FROM USE OF OXAYDO

See full prescribing information for complete boxed warning.

- OXAYDO exposes users to risks of addiction, abuse, and misuse, which can lead to overdose and death. Assess patient’s risk before prescribing and reassess regularly for these behaviors and conditions. (5.1)
- Serious, life-threatening, or fatal respiratory depression may occur, especially during initiation or following a dosage increase. To reduce the risk of respiratory depression, proper dosing and titration of OXAYDO are essential. (5.2)
- Accidental ingestion of OXAYDO, especially by children, can result in a fatal overdose of oxycodone. (5.2)
- Concomitant use of opioids with benzodiazepines or other central nervous system (CNS) depressants, including alcohol, may result in profound sedation, respiratory depression, coma, and death. Reserve concomitant prescribing for use in patients for whom alternative treatment options are inadequate. (5.6, 7)
- Advise pregnant women using opioids for an extended period of time of the risk of Neonatal Opioid Withdrawal Syndrome, which may be life-threatening if not recognized and treated. Ensure that management by neonatology experts will be available at delivery. (5.4)
- Healthcare providers are strongly encouraged to complete a REMS-compliant education program and to counsel patients and caregivers on serious risks, safe use, and the importance of reading the Medication Guide with each prescription. (5.5)
- Concomitant use with CYP3A4 inhibitors (or discontinuation of CYP3A4 inducers) can result in a fatal overdose of oxycodone. (5.6, 7, 12.3)

1 INDICATIONS AND USAGE

OXAYDO is an opioid agonist indicated for the management of acute and chronic pain severe enough to require an opioid analgesic and for which alternative treatments are inadequate. (1)

Limitations of Use (1)

Because of the risks of addiction, abuse, misuse, overdose, and death, which can occur at any dosage or duration and persist over the course of therapy, reserve opioid analgesics, including OXAYDO, for use in patients for whom alternative treatment options are ineffective, not tolerated, or would be otherwise inadequate to provide sufficient management of pain. (1, 5.1)

2 DOSAGE AND ADMINISTRATION

- OXAYDO should be prescribed only by healthcare professionals who are knowledgeable about the use of opioids and how to mitigate the associated risks. (2.1)
- Use the lowest effective dosage for the shortest duration of time consistent with individual patient treatment goals. Reserve titration to higher doses of OXAYDO for patients in whom lower doses are insufficiently effective and in whom the expected benefits of using a higher dose opioid clearly outweigh the substantial risks. (2.1, 5)
- Many acute pain conditions (e.g., the pain that occurs with a number of surgical procedures or acute musculoskeletal injuries) require no more than a few days of an opioid analgesic. Clinical guidelines on opioid prescribing for some acute pain conditions are available. (2.1)
- Initiate the dosing regimen for each patient individually, taking into account the patient’s underlying cause and severity of pain, prior analgesic treatment and response, and risk factors for addiction, abuse, and misuse. (2.1, 5.1)
- Respiratory depression can occur at any time during opioid therapy, especially when initiating and following dosage increases with OXAYDO. Consider this risk when selecting an initial dose and when making dose adjustments. (2.1, 5.2)
- Discuss opioid overdose reversal agents and options for acquiring them with the patient and/or caregiver, both when initiating and renewing treatment with OXAYDO, especially if the patient has additional risk factors for overdose, or close contacts at risk for exposure and overdose. (2.2, 5.1, 5.2, 5.3)
- For opioid naïve patients, initiate treatment with 5 mg to 15 mg every 4 to 6 hours as needed for pain, and at the lowest dose necessary to achieve adequate analgesia. Titrate the dose based upon the individual patient’s response to their initial dose of OXAYDO. (2.2, 2.4)
- Must be swallowed whole and is not amenable to crushing and dissolution. Do not use OXAYDO for administration via nasogastric, gastric, or other feeding tubes as it may cause obstruction of feeding tubes (2.1, 17)
- Must take tablets one at a time, with enough water to ensure complete swallowing immediately after placing in mouth. (2.1)
- Periodically reassess patients receiving OXAYDO to evaluate the continued need for opioid analgesics to maintain pain control, for the signs or symptoms of adverse reactions, and for the development of addiction, abuse, or misuse. (2.4)
- Do not rapidly reduce or abruptly discontinue OXAYDO in a physically-dependent patient because rapid reduction or abrupt discontinuation of opioid analgesics has resulted in serious withdrawal symptoms, uncontrolled pain, and suicide. (2.4, 5.14)

3 DOSAGE FORMS AND STRENGTHS

Tablets: 5 mg and 7.5 mg oxycodone HCl (3)

4 CONTRAINDICATIONS

- Significant respiratory depression. (4)
- Acute or severe bronchial asthma in an unmonitored setting or in absence of resuscitative equipment. (4)
- Known or suspected gastrointestinal obstruction, including paralytic ileus. (4)
- Hypersensitivity to oxycodone, oxycodone salts, or any components of the product. (4)

5 WARNINGS AND PRECAUTIONS

- Opioid-Induced Hyperalgesia and Allodynia: Opioid-Induced Hyperalgesia (OIH) occurs when an opioid analgesic paradoxically causes an increase in pain, or an increase in sensitivity to pain. If OIH is suspected, carefully consider appropriately decreasing the dose of the current opioid analgesic, or opioid rotation. (5.7)
- Life-Threatening Respiratory Depression in Patients with Chronic Pulmonary Disease or in Elderly, Cachectic, or Debilitated Patients: Regularly evaluate, particularly during initiation and titration. (5.8)
- Adrenal Insufficiency: If diagnosed, treat with physiologic replacement of corticosteroids, and wean patient off of the opioid. (5.9)
- Severe Hypotension: Regularly evaluate during dosage initiation and titration. Avoid use of OXAYDO in patients with circulatory shock. (5.10)
- Risks of Use in Patients with Increased Intracranial Pressure, Brain Tumors, Head Injury, or Impaired Consciousness: Monitor for sedation and respiratory depression. Avoid use of OXAYDO in patients with impaired consciousness or coma. (5.11)

6 ADVERSE REACTIONS

Most common adverse reactions (incidence ≥3%) were nausea, constipation, vomiting, headache, pruritus, insomnia, dizziness, asthenia, and somnolence. (6.1)

To report SUSPECTED ADVERSE REACTIONS, contact Zyla Life Sciences US Inc. at 1-800-518-1084 or FDA at 1-800-FDA-1088 or www.fda.gov/medwatch.

7 DRUG INTERACTIONS

- Serotonergic Drugs: Concomitant use may result in serotonin syndrome. Discontinue OXAYDO if serotonin syndrome is suspected. (7)
- Monoamine Oxidase Inhibitors (MAOIs): Can potentiate the effects of oxycodone. Avoid concomitant use in patients receiving MAOIs or within 14 days of stopping treatment with an MAOI. (7)
- Mixed Agonist/Antagonist Analgesics: Avoid use with OXAYDO because they may reduce analgesic effect of OXAYDO or precipitate withdrawal symptoms. (7)

8 USE IN SPECIFIC POPULATIONS

- Pregnancy: May cause fetal harm. (8.1)

FULL PRESCRIBING INFORMATION

WARNING: SERIOUS AND LIFE-THREATENING RISKS FROM USE OF OXAYDO

Addiction, Abuse, and Misuse

Because the use of OXAYDO exposes patients and other users to the risks of opioid addiction, abuse, and misuse, which can lead to overdose and death, assess each patient’s risk prior to prescribing and reassess all patients regularly for the development of these behaviors and conditions [see Warnings and Precautions (5.1)].

Life-Threatening Respiratory Depression

Serious, life-threatening, or fatal respiratory depression may occur with use of OXAYDO, especially during initiation or following a dosage increase. To reduce the risk of respiratory depression, proper dosing and titration of OXAYDO are essential [see Warnings and Precautions (5.2)].

Accidental Ingestion

Accidental ingestion of even one dose of OXAYDO, especially by children, can result in a fatal overdose of oxycodone [see Warnings and Precautions (5.2)].

Risks From Concomitant Use With Benzodiazepines Or Other CNS Depressants

Concomitant use of opioids with benzodiazepines or other central nervous system (CNS) depressants, including alcohol, may result in profound sedation, respiratory depression, coma, and death. Reserve concomitant prescribing of OXAYDO and benzodiazepines or other CNS depressants for use in patients for whom alternative treatment options are inadequate [see Warnings and Precautions (5.3), Drug Interactions (7)].

Neonatal Opioid Withdrawal Syndrome (NOWS)
Advise pregnant women using opioids for an extended period of time of the risk of Neonatal Opioid Withdrawal Syndrome, which may be life-threatening if not recognized and treated. Ensure that management by neonatology experts will be available at delivery [see Warnings and Precautions (5.4)].

Opioid Analgesic Risk Evaluation and Mitigation Strategy (REMS)

Healthcare providers are strongly encouraged to complete a REMS-compliant education program and to counsel patients and caregivers on serious risks, safe use, and the importance of reading the Medication Guide with each prescription [see Warnings and Precautions (5.5)].

Cytochrome P450 3A4 Interaction

The concomitant use of OXAYDO with all cytochrome P450 3A4 inhibitors may result in an increase in oxycodone plasma concentrations, which could increase or prolong adverse reactions and may cause potentially fatal respiratory depression. In addition, discontinuation of a concomitantly used cytochrome P450 3A4 inducer may result in an increase in oxycodone plasma concentration. Regularly evaluate patients receiving OXAYDO and any CYP3A4 inhibitor or inducer [see Warnings and Precautions (5.6), Drug Interactions (7), Clinical Pharmacology (12.3)].

1 INDICATIONS AND USAGE

OXAYDO is indicated for the management of acute and chronic pain severe enough to require an opioid analgesic and for which alternative treatments are inadequate.

Limitations of Use

Because of the risks of addiction, abuse, misuse, overdose, and death, which can occur at any dosage or duration and persist over the course of therapy [see Warnings and Precautions (5.1)], reserve opioid analgesics, including OXAYDO, for use in patients for whom alternative treatment options are ineffective, not tolerated, or would be otherwise inadequate to provide sufficient management of pain.

2 DOSAGE AND ADMINISTRATION

2.1 Important Dosage and Administration Instructions

- OXAYDO should be prescribed only by healthcare professionals who are knowledgeable about the use of opioids and how to mitigate the associated risks.
- Use the lowest effective dosage for the shortest duration of time consistent with individual patient treatment goals [see Warnings and Precautions (5)]. Because the risk of overdose increases as opioid doses increase, reserve titration to higher doses of OXAYDO for patients in whom lower doses are insufficiently effective and in whom the expected benefits of using a higher dose opioid clearly outweigh the substantial risks.
- Many acute pain conditions (e.g., the pain that occurs with a number of surgical procedures or acute musculoskeletal injuries) require no more than a few days of an opioid analgesic. Clinical guidelines on opioid prescribing for some acute pain conditions are available.
- There is variability in the opioid analgesic dose and duration needed to adequately manage pain due both to the cause of pain and to individual patient factors. Initiate the dosing regimen for each patient individually, taking into account the patient’s underlying cause and severity of pain, prior analgesic treatment and response, and risk factors for addiction, abuse, and misuse [see Warnings and Precautions (5.1)].
- Respiratory depression can occur at any time during opioid therapy, especially when initiating and following dosage increases with OXAYDO. Consider this risk when selecting an initial dose and when making dose adjustments [see Warnings and Precautions (5.2)].
- OXAYDO must be swallowed whole. Take each tablet with enough water to ensure complete swallowing immediately after placing in the mouth.
- OXAYDO is not amenable to crushing and dissolution. Do not administer OXAYDO via nasogastric, gastric or other feeding tubes as it may cause obstruction of feeding tubes.

2.2 Patient Access to an Opioid Overdose Reversal Agent for the Emergency Treatment of Opioid Overdose

Inform patients and caregivers about opioid overdose reversal agents (e.g., naloxone, nalmefene). Discuss the importance of having access to an opioid overdose reversal agent, especially if the patient has risk factors for overdose (e.g., concomitant use of CNS depressants, a history of opioid use disorder, or prior opioid overdose) or if there are household members (including children) or other close contacts at risk for accidental ingestion or opioid overdose. The presence of risk factors for overdose should not prevent the management of pain in any patient [see Warnings and Precautions (5.1, 5.2, 5.3)].

Discuss the options for obtaining an opioid overdose reversal agent (e.g., prescription, over-the-counter, or as part of a community-based program) [see Warnings and Precautions (5.2)].

There are important differences among the opioid overdose reversal agents, such as route of administration, product strength, approved patient age range, and pharmacokinetics. Be familiar with these differences, as outlined in the approved labeling for those products, prior to recommending or prescribing such an agent.

2.3 Initial Dosage

Although it is not possible to list every condition that is important to the selection of the initial dose of OXAYDO, attention must be given to:

1. the daily dose, potency and characteristics of a full agonist or mixed agonist/antagonist the patient has been taking previously
2. the reliability of the relative potency estimate to calculate the dose of oxycodone HCl needed
3. the degree of opioid tolerance
4. the general condition and medical status of the patient, including the patient’s weight and age
5. the balance between pain management and adverse reactions
6. the type and severity of the patient’s pain
7. risk factors for abuse or addiction, including a prior history of abuse or addiction

Use of OXAYDO as the First Opioid Analgesic

Initiate treatment with OXAYDO in a dosing range of 5 mg to 15 mg every 4 to 6 hours as needed for pain, and at the lowest dose necessary to achieve adequate analgesia. Titrate the dose based upon the individual patient’s response to their initial dose of OXAYDO.

Conversion from Other Opioids to OXAYDO

There is inter-patient variability in the potency of opioid drugs and opioid formulations. Therefore, a conservative approach is advised when determining the total daily dosage of OXAYDO. It is safer to underestimate a patient’s 24-hour OXAYDO dosage than to overestimate the 24-hour OXAYDO dosage and manage an adverse reaction due to overdose. If a patient has been receiving opioid-containing medications prior to taking OXAYDO, the potency of the prior opioid relative to oxycodone should be factored into the selection of the total daily dose (TDD) of oxycodone.

In converting patients from other opioids to Oxycodone Hydrochloride Capsules, close observation and adjustment of dosage based upon the patient’s response to OXAYDO is imperative. Administration of supplemental analgesia for breakthrough or incident pain and titration of the total daily dose of OXAYDO may be necessary, especially in patients who have disease states that are changing rapidly.

Conversion from Fixed-Ratio Oral Opioid/Non-Opioid Combinations

When converting patients from fixed-ratio opioid/non-opioid drug regimens to OXAYDO, determine whether or not to continue the non-opioid analgesic. Titrate the dose of OXAYDO in response to the level of analgesia and adverse reactions afforded by the dosing regimen regardless of whether the non-opioid is continued.

Conversion from Other Oral Opioid Therapy to OXAYDO

If a patient has been receiving opioid-containing medications prior to taking OXAYDO, factor the potency of the prior opioid relative to oxycodone into the selection of the total daily dose of oxycodone.

In converting patients from other opioids to OXAYDO, close observation and adjustment of dosage based upon the patient's response to OXAYDO is imperative.

Conversion from OXAYDO to Extended-Release Oxycodone

The relative bioavailability of OXAYDO compared to extended-release oxycodone is unknown, so conversion to extended-release tablets may lead to increased risk of excessive sedation and respiratory depression.

2.4 Titration and Maintenance of Therapy

Individually titrate OXAYDO to a dose that provides adequate analgesia and minimizes adverse reactions. Continually reevaluate patients receiving OXAYDO to assess the maintenance of pain control, signs and symptoms of opioid withdrawal, and other adverse reactions, as well as to reassess for the development of addiction, abuse, or misuse [see Warnings and Precautions (5.1, 5.14)]. Frequent communication is important among the prescriber, other members of the healthcare team, the patient, and the caregiver/family during periods of changing analgesic requirements, including initial titration.

If the level of pain increases after dosage stabilization, attempt to identify the source of increased pain before increasing the dosage of OXAYDO. If after increasing the dosage, unacceptable opioid-related adverse reactions are observed (including an increase in pain after a dosage increase), consider reducing the dosage [see Warnings and Precautions (5)]. Adjust the dosage to obtain an appropriate balance between management of pain and opioid-related adverse reactions.

2.5 Safe Reduction or Discontinuation of OXAYDO

Do not rapidly reduce or abruptly discontinue OXAYDO in patients who may be physically dependent on opioids. Rapid reduction or abrupt discontinuation of opioid analgesics in patients who are physically dependent on opioids has resulted in serious withdrawal symptoms, uncontrolled pain, and suicide. Rapid reduction or abrupt discontinuation has also been associated with attempts to find other sources of opioid analgesics, which may be confused with drug-seeking for abuse. Patients may also attempt to treat their pain or withdrawal symptoms with illicit opioids, such as heroin, and other substances.

When a decision has been made to decrease the dose or discontinue therapy in an opioid-dependent patient taking OXAYDO, there are a variety of factors that should be considered, including the total daily dose of opioid (including OXAYDO) the patient has been taking, the duration of treatment, the type of pain being treated, and the physical and psychological attributes of the patient. It is important to ensure ongoing care of the patient and to agree on an appropriate tapering schedule and follow-up plan so that patient and provider goals and expectations are clear and realistic. When opioid analgesics are being discontinued due to a suspected substance use disorder, evaluate and treat the patient, or refer for evaluation and treatment of the substance use disorder. Treatment should include evidence-based approaches, such as medication assisted treatment of opioid use disorder. Complex patients with comorbid pain and substance use disorders may benefit from referral to a specialist.

There are no standard opioid tapering schedules that are suitable for all patients. Good clinical practice dictates a patient-specific plan to taper the dose of the opioid gradually. For patients on OXAYDO who are physically opioid-dependent, initiate the taper by a small enough increment (e.g., no greater than 10% to 25% of the total daily dose) to avoid withdrawal symptoms, and proceed with dose-lowering at an interval of every 2 to 4 weeks. Patients who have been taking opioids for briefer periods of time may tolerate a more rapid taper.

It may be necessary to provide the patient with lower dosage strengths to accomplish a successful taper. Reassess the patient frequently to manage pain and withdrawal symptoms, should they emerge. Common withdrawal symptoms include restlessness, lacrimation, rhinorrhea, yawning, perspiration, chills, myalgia, and mydriasis. Other signs and symptoms also may develop, including irritability, anxiety, backache, joint pain, weakness, abdominal cramps, insomnia, nausea, anorexia, vomiting, diarrhea, or increased blood pressure, respiratory rate, or heart rate. If withdrawal symptoms arise, it may be necessary to pause the taper for a period of time or raise the dose of the opioid analgesic to the previous dose and then proceed with a slower taper. In addition, evaluate patients for any changes in mood, emergence of suicidal thoughts, or use of other substances.

When managing patients taking opioid analgesics, particularly those who have been treated for an extended period of time and/or with high doses for chronic pain, ensure a multimodal approach to pain management, including mental health support (if needed), is in place prior to initiating an opioid analgesic taper. A multimodal approach to pain management may optimize the treatment of chronic pain, as well as assist with the successful tapering of the opioid analgesic [see Warnings and Precautions (5.14), Drug Abuse and Dependence (9.3)].

3 DOSAGE FORMS AND STRENGTHS

Tablets: 5 mg and 7.5 mg of oxycodone HCl, USP:

Strength | Description
5 mg | Round, convex, white tablet, debossed “5” on one side, letter “O” on other side.
7.5 mg | Round, convex, white tablet, debossed “7.5” on one side, letter “O” on other side.

4 CONTRAINDICATIONS

OXAYDO is contraindicated in patients with:

- Significant respiratory depression [see Warnings and Precautions (5.2)]
- Acute or severe bronchial asthma in an unmonitored setting or in the absence of resuscitative equipment [see Warnings and Precautions (5.8)]
- Known or suspected gastrointestinal obstruction, including paralytic ileus [see Warnings and Precautions (5.12)]
- Hypersensitivity to oxycodone, oxycodone salts, or any components of the product (e.g., anaphylaxis) [see Adverse Reactions (6.2)]

5 WARNINGS AND PRECAUTIONS

5.1 Addiction, Abuse, and Misuse

OXAYDO contains oxycodone, a Schedule II controlled substance. As an opioid, OXAYDO exposes users to the risks of addiction, abuse, and misuse [see Drug Abuse and Dependence (9)].

Although the risk of addiction in any individual is unknown, it can occur in patients appropriately prescribed OXAYDO. Addiction can occur at recommended dosages and if the drug is misused or abused. The risk of opioid-related overdose or overdose-related death is increased with higher opioid doses, and this risk persists over the course of therapy. In postmarketing studies, addiction, abuse, misuse, and fatal and non-fatal opioid overdose were observed in patients with long-term opioid use [see Adverse Reactions (6.2)].

Assess each patient’s risk for opioid addiction, abuse, or misuse prior to prescribing OXAYDO, and reassess all patients receiving OXAYDO for the development of these behaviors and conditions. Risks are increased in patients with a personal or family history of substance abuse (including drug or alcohol abuse or addiction) or mental illness (e.g., major depression). The potential for these risks should not, however, prevent the proper management of pain in any given patient. Patients at increased risk may be prescribed opioids such as OXAYDO but use in such patients necessitates intensive counseling about the risks and proper use of OXAYDO along with frequent reevaluation for signs of addiction, abuse, and misuse. Consider recommending or prescribing an opioid overdose reversal agent [see Dosage and Administration (2.2), Warnings and Precautions (5.2)].

Opioids are sought for nonmedical use and are subject to diversion from legitimate prescribed use. Consider these risks when prescribing or dispensing OXAYDO. Strategies to reduce these risks include prescribing the drug in the smallest appropriate quantity and advising the patient on careful storage of the drug during the course of treatment and on the proper disposal of unused drug. Contact the local state professional licensing board or state-controlled substances authority for information on how to prevent and detect abuse or diversion of this product.

5.2 Life-Threatening Respiratory Depression

Serious, life-threatening, or fatal respiratory depression has been reported with the use of opioids, even when used as recommended. Respiratory depression, if not immediately recognized and treated, may lead to respiratory arrest and death. Management of respiratory depression may include close observation, supportive measures, and use of opioid overdose reversal agents, depending on the patient’s clinical status [see Overdosage (10)]. Carbon dioxide (CO2) retention from opioid-induced respiratory depression can exacerbate the sedating effects of opioids.

While serious, life-threatening, or fatal respiratory depression can occur at any time during the use of OXAYDO, the risk is greatest during the initiation of therapy or following a dosage increase.

To reduce the risk of respiratory depression, proper dosing and titration of OXAYDO are essential [see Dosage and Administration (2)]. Overestimating the OXAYDO dosage when converting patients from another opioid product can result in a fatal overdose with the first dose.

Accidental ingestion of even one dose of OXAYDO, especially by children, can result in respiratory depression and death due to an overdose of oxycodone.

Educate patients and caregivers on how to recognize respiratory depression and emphasize the importance of calling 911 or getting emergency medical help right away in the event of a known or suspected overdose.

Opioids can cause sleep-related breathing disorders including central sleep apnea (CSA) and sleep-related hypoxemia. Opioid use increases the risk of CSA in a dose-dependent fashion. In patients who present with CSA, consider decreasing the opioid dosage using best practices for opioid taper [see Dosage and Administration (2.4)].

Patient Access to an Opioid Overdose Reversal Agent for the Emergency Treatment of Opioid Overdose

Inform patients and caregivers about opioid overdose reversal agents (e.g., naloxone, nalmefene). Discuss the importance of having access to an opioid overdose reversal agent, especially if the patient has risk factors for overdose (e.g., concomitant use of CNS depressants, a history of opioid use disorder, or prior opioid overdose) or if there are household members (including children) or other close contacts at risk for accidental ingestion or opioid overdose. The presence of risk factors for overdose should not prevent the management of pain in any patient [see Warnings and Precautions (5.1, 5.3)].

Discuss the options for obtaining an opioid overdose reversal agent (e.g., prescription, over-the-counter, or as part of a community-based program).

There are important differences among the opioid overdose reversal agents, such as route of administration, product strength, approved patient age range, and pharmacokinetics. Be familiar with these differences, as outlined in the approved labeling for those products, prior to recommending or prescribing such an agent.

Educate patients and caregivers on how to recognize respiratory depression, and how to use an opioid overdose reversal agent for the emergency treatment of opioid overdose. Emphasize the importance of calling 911 or getting emergency medical help, even if an opioid overdose reversal agent is administered [see Dosage and Administration (2.2), Warnings and Precautions (5.1, 5.3), Overdosage (10)].

5.3 Risks from Concomitant Use with Benzodiazepines or Other CNS Depressants

Profound sedation, respiratory depression, coma, and death may result from the concomitant use of OXAYDO with benzodiazepines and/or other CNS depressants, including alcohol (e.g., non-benzodiazepine sedatives/hypnotics, anxiolytics, tranquilizers, muscle relaxants, general anesthetics, antipsychotics, gabapentinoids [gabapentin or pregabalin], other opioids, alcohol). Because of these risks, reserve concomitant prescribing of these drugs for use in patients for whom alternative treatment options are inadequate.

Observational studies have demonstrated that concomitant use of opioid analgesics and benzodiazepines increases the risk of drug-related mortality compared to use of opioid analgesics alone. Because of similar pharmacological properties, it is reasonable to expect similar risk with the concomitant use of other CNS depressant drugs with opioid analgesics [see Drug Interactions (7)].

If the decision is made to prescribe a benzodiazepine or other CNS depressant concomitantly with an opioid analgesic, prescribe the lowest effective dosages and minimum durations of concomitant use. In patients already receiving an opioid analgesic, prescribe a lower initial dose of the benzodiazepine or other CNS depressant than indicated in the absence of an opioid, and titrate based on clinical response. If an opioid analgesic is initiated in a patient already taking a benzodiazepine or other CNS depressant, prescribe a lower initial dose of the opioid analgesic, and titrate based on clinical response. Inform patients and caregivers of this potential interaction and educate them on the signs and symptoms of respiratory depression (including sedation).

If concomitant use is warranted, consider recommending or prescribing an opioid overdose reversal agent [see Dosage and Administration (2.2), Warnings and Precautions (5.3), Overdosage (10)].

Advise both patients and caregivers about the risks of respiratory depression and sedation when OXAYDO is used with benzodiazepines or other CNS depressants (including alcohol and illicit drugs). Advise patients not to drive or operate heavy machinery until the effects of concomitant use of the benzodiazepine or other CNS depressant have been determined. Screen patients for risk of substance use disorders, including opioid abuse and misuse, and warn them of the risk for overdose and death associated with the use of additional CNS depressants including alcohol and illicit drugs [see Drug Interactions (7)].

5.4 Neonatal Opioid Withdrawal Syndrome

Use of OXAYDO for an extended period of time during pregnancy can result in withdrawal in the neonate. Neonatal opioid withdrawal syndrome, unlike opioid withdrawal syndrome in adults, may be life-threatening if not recognized and treated, and requires management according to protocols developed by neonatology experts. Observe newborns for signs of neonatal opioid withdrawal syndrome and manage accordingly. Advise pregnant women using opioids for an extended period of time of the risk of neonatal opioid withdrawal syndrome and ensure that appropriate treatment will be available [see Use in Specific Populations (8.1)].

5.5 Opioid Analgesic Risk Evaluation and Mitigation Strategy (REMS)

To ensure that the benefits of opioid analgesics outweigh the risks of addiction, abuse, and misuse, the Food and Drug Administration (FDA) has required a Risk Evaluation and Mitigation Strategy (REMS) for these products. Under the requirements of the REMS, drug companies with approved opioid analgesic products must make REMS-compliant education programs available to healthcare providers. Healthcare providers are strongly encouraged to do all of the following:

• Complete a REMS-compliant education program offered by an accredited provider of continuing education (CE) or another education program that includes all the elements of the FDA Education Blueprint for Health Care Providers Involved in the Management or Support of Patients with Pain.

• Discuss the safe use, serious risks, and proper storage and disposal of opioid analgesics with patients and/or their caregivers every time these medicines are prescribed. The Patient Counseling Guide (PCG) can be obtained at this link: www.fda.gov/OpioidAnalgesicREMSPCG.

• Emphasize to patients and their caregivers the importance of reading the Medication Guide that they will receive from their pharmacist every time an opioid analgesic is dispensed to them.

• Consider using other tools to improve patient, household, and community safety, such as patient- prescriber agreements that reinforce patient-prescriber responsibilities.

To obtain further information on the opioid analgesic REMS and for a list of accredited REMS CME/CE, call 1-800-503-0784, or log on to www.opioidanalgesicrems.com. The FDA Blueprint can be found at www.fda.gov/OpioidAnalgesicREMSBlueprint.

5.6 Risks of Concomitant Use or Discontinuation of Cytochrome P450 3A4 Inhibitors and Inducers

Concomitant use of OXAYDO with a CYP3A4 inhibitor, such as macrolide antibiotics (e.g., erythromycin), azole-antifungal agents (e.g., ketoconazole), and protease inhibitors (e.g., ritonavir), may increase plasma concentrations of oxycodone and prolong opioid adverse reactions, which may cause potentially fatal respiratory depression [see Warnings and Precautions (5.3)], particularly when an inhibitor is added after a stable dose of OXAYDO is achieved. Similarly, discontinuation of a CYP3A4 inducer, such as rifampin, carbamazepine, and phenytoin, in OXAYDO-treated patients may increase oxycodone plasma concentrations and prolong opioid adverse reactions. When using OXAYDO with CYP3A4 inhibitors or discontinuing CYP3A4 inducers in OXAYDO-treated patients, evaluate patients at frequent intervals and consider dosage reduction of OXAYDO until stable drug effects are achieved [see Drug Interactions (7)].

Concomitant use of OXAYDO with CYP3A4 inducers or discontinuation of a CYP3A4 inhibitor could decrease oxycodone plasma concentrations, decrease opioid efficacy or, possibly, lead to a withdrawal syndrome in a patient who had developed physical dependence to oxycodone. When using OXAYDO with CYP3A4 inducers or discontinuing CYP3A4 inhibitors, evaluate patients closely at frequent intervals and consider increasing the opioid dosage if needed to maintain adequate analgesia or if symptoms of opioid withdrawal occur [see Drug Interactions (7)].

5.7 Opioid-Induced Hyperalgesia and Allodynia

Opioid-Induced Hyperalgesia (OIH) occurs when an opioid analgesic paradoxically causes an increase in pain, or an increase in sensitivity to pain. This condition differs from tolerance, which is the need for increasing doses of opioids to maintain a defined effect [see Dependence (9.3)]. Symptoms of OIH include (but may not be limited to) increased levels of pain upon opioid dosage increase, decreased levels of pain upon opioid dosage decrease, or pain from ordinarily non-painful stimuli (allodynia). These symptoms may suggest OIH only if there is no evidence of underlying disease progression, opioid tolerance, opioid withdrawal, or addictive behavior.

Cases of OIH have been reported, both with short-term and longer-term use of opioid analgesics. Though the mechanism of OIH is not fully understood, multiple biochemical pathways have been implicated. Medical literature suggests a strong biologic plausibility between opioid analgesics and OIH and allodynia. If a patient is suspected to be experiencing OIH, carefully consider appropriately decreasing the dose of the current opioid analgesic or opioid rotation (safely switching the patient to a different opioid moiety) [see Dosage and Administration (2.5), Warnings and Precautions (5.14)].

5.8 Life-Threatening Respiratory Depression in Patients with Chronic Pulmonary Disease or in Elderly, Cachectic, or Debilitated Patients

The use of OXAYDO in patients with acute or severe bronchial asthma in an unmonitored setting or in the absence of resuscitative equipment is contraindicated.

Patients with Chronic Pulmonary Disease: OXAYDO-treated patients with significant chronic obstructive pulmonary disease or cor pulmonale, and those with a substantially decreased respiratory reserve, hypoxia, hypercapnia, or pre-existing respiratory depression are at increased risk of decreased respiratory drive including apnea, even at recommended dosages of OXAYDO [see Warnings and Precautions (5.2)].

Elderly, Cachectic, or Debilitated Patients: Life-threatening respiratory depression is more likely to occur in elderly, cachectic, or debilitated patients because they may have altered pharmacokinetics or altered clearance compared to younger, healthier patients [see Warnings and Precautions (5.2)].

Regularly evaluate patients, particularly when initiating and titrating OXAYDO and when OXAYDO is given concomitantly with other drugs that depress respiration [see Warnings and Precautions (5.2, 5.3)].

Alternatively, consider the use of non-opioid analgesics in these patients.

5.9 Adrenal Insufficiency

Cases of adrenal insufficiency have been reported with opioid use, more often following greater than one month of use. Presentation of adrenal insufficiency may include non-specific symptoms and signs including nausea, vomiting, anorexia, fatigue, weakness, dizziness, and low blood pressure. If adrenal insufficiency is suspected, confirm the diagnosis with diagnostic testing as soon as possible. If adrenal insufficiency is diagnosed, treat with physiologic replacement doses of corticosteroids. Wean the patient off of the opioid to allow adrenal function to recover and continue corticosteroid treatment until adrenal function recovers. Other opioids may be tried as some cases reported use of a different opioid without recurrence of adrenal insufficiency. The information available does not identify any particular opioids as being more likely to be associated with adrenal insufficiency.

5.10 Severe Hypotension

OXAYDO may cause severe hypotension including orthostatic hypotension and syncope in ambulatory patients. There is increased risk in patients whose ability to maintain blood pressure has already been compromised by a reduced blood volume or concurrent administration of certain CNS depressant drugs (e.g., phenothiazines or general anesthetics) [see Drug Interactions (7)]. Regularly evaluate these patients for signs of hypotension after initiating or titrating the dosage of OXAYDO. In patients with circulatory shock, OXAYDO may cause vasodilation that can further reduce cardiac output and blood pressure. Avoid the use of OXAYDO in patients with circulatory shock.

5.11 Risks of Use in Patients with Increased Intracranial Pressure, Brain Tumors, Head Injury, or Impaired Consciousness

In patients who may be susceptible to the intracranial effects of CO2 retention (e.g., those with evidence of increased intracranial pressure or brain tumors), OXAYDO may reduce respiratory drive, and the resultant CO2 retention can further increase intracranial pressure. Monitor such patients for signs of sedation and respiratory depression, particularly when initiating therapy with OXAYDO.

Opioids may also obscure the clinical course in a patient with a head injury. Avoid the use of OXAYDO in patients with impaired consciousness or coma.

5.12 Risks of Gastrointestinal Complications

OXAYDO is contraindicated in patients with known or suspected gastrointestinal obstruction, including paralytic ileus.

The oxycodone in OXAYDO may cause spasm of the sphincter of Oddi. Opioids may cause increases in serum amylase. Regularly evaluate patients with biliary tract disease, including acute pancreatitis, for worsening symptoms.

Cases of opioid-induced esophageal dysfunction (OIED) have been reported in patients taking opioids. The risk of OIED may increase as the dose and/or duration of opioids increases. Regularly evaluate patients for signs and symptoms of OIED (e.g., dysphagia, regurgitation, non-cardiac chest pain), and if necessary, adjust opioid therapy as clinically appropriate [see Clinical Pharmacology (12.2)].

5.13 Increased Risk of Seizures in Patients with Seizure Disorders

The oxycodone in OXAYDO may increase the frequency of seizures in patients with seizure disorders and may increase the risk of seizures occurring in other clinical settings associated with seizures. Regularly evaluate patients with a history of seizure disorders for worsened seizure control during OXAYDO therapy.

5.14 Withdrawal

Do not rapidly reduce or abruptly discontinue OXAYDO in a patient physically dependent on opioids. When discontinuing OXAYDO in a physically dependent patient, gradually taper the dosage. Rapid tapering of OXAYDO in a patient physically dependent on opioids may lead to a withdrawal syndrome and return of pain [see Dosage and Administration (2.5), Drug Abuse and Dependence (9.3)].

Additionally, avoid the use of mixed agonist/antagonist (e.g., pentazocine, nalbuphine, and butorphanol) or partial agonist (e.g., buprenorphine) analgesics in patients who are receiving a full opioid agonist analgesic, including OXAYDO. In these patients, mixed agonist/antagonist and partial agonist analgesics may reduce the analgesic effect and/or precipitate withdrawal symptoms [see Drug Interactions (7)].

5.15 Risks of Driving and Operating Machinery

OXAYDO may impair the mental or physical abilities needed to perform potentially hazardous activities such as driving a car or operating machinery. Warn patients not to drive or operate dangerous machinery unless they are tolerant to the effects of OXAYDO and know how they will react to the medication.

6 ADVERSE REACTIONS

The following serious adverse reactions are described, or described in greater detail, in other sections:

- Addiction, Abuse, and Misuse [see Warnings and Precautions (5.1)]
- Life-Threatening Respiratory Depression [see Warnings and Precautions (5.2)]
- Interactions with Benzodiazepines or Other CNS Depressants [see Warnings and Precautions (5.3)]
- Neonatal Opioid Withdrawal Syndrome [see Warnings and Precautions (5.4)]
- Opioid-Induced Hyperalgesia and Allodynia [see Warnings and Precautions (5.7)]
- Adrenal Insufficiency [see Warnings and Precautions (5.9)]
- Severe Hypotension [see Warnings and Precautions (5.10)]
- Gastrointestinal Adverse Reactions [see Warnings and Precautions (5.12)]
- Seizures [see Warnings and Precautions (5.13)]
- Withdrawal [see Warnings and Precautions (5.14)]

6.1 Clinical Trials Experience

Because clinical trials are conducted under widely varying conditions, the adverse reaction rates observed in the clinical trials of a drug cannot be directly compared to rates in the clinical trials of another drug and may not reflect the rates observed in clinical practice.

Serious adverse reactions that may be associated with OXAYDO include: respiratory depression, respiratory arrest, circulatory depression, cardiac arrest, hypotension, and/or shock [see Warnings and Precautions (5) and Overdosage (10)].

The common adverse reactions seen on initiation of therapy with OXAYDO are dose-dependent, and their frequency depends on the clinical setting, the patient’s level of opioid tolerance, and host factors specific to the individual. They should be expected and managed as a part of opioid therapy. The most frequent of the adverse reactions include nausea, constipation, vomiting, headache, and pruritus.

The frequency of adverse reactions during initiation of opioid therapy may be minimized by careful individualization of starting dosage, slow titration and the avoidance of large rapid swings in plasma concentration of the opioid. Many of these adverse reactions will abate as therapy is continued and some degree of tolerance is developed, but others may be expected to remain throughout therapy.

In all patients for whom dosing information was available (n=191) from open-label and double-blind studies involving oxycodone, the following adverse reactions were recorded in oxycodone-treated patients with an incidence of ≥3%. In descending order of frequency they were: nausea, constipation, vomiting, headache, pruritus, insomnia, dizziness, asthenia, and somnolence.

The following adverse reactions occurred in less than 3% of patients involved in clinical trials with oxycodone:

Body as a Whole: abdominal pain, accidental injury, allergic reaction, back pain, chills and fever, fever, flu syndrome, infection, neck pain, pain, photosensitivity reaction, and sepsis.

Cardiovascular: deep vein thrombophlebitis, heart failure, hemorrhage, hypotension, migraine, palpitation, and tachycardia.

Digestive: anorexia, diarrhea, dyspepsia, dysphagia, gingivitis, glossitis, and nausea and vomiting.

Hematopoietic and Lymphatic: anemia and leukopenia.

Metabolism and Nutrition: edema, gout, hyperglycemia, iron deficiency anemia, and peripheral edema.

Musculoskeletal: arthralgia, arthritis, bone pain, myalgia, and pathological fracture.

Nervous System: agitation, anxiety, confusion, dry mouth, hypertonia, hypesthesia, nervousness, neuralgia, personality disorder, tremor, and vasodilation.

Respiratory: bronchitis, cough increased, dyspnea, epistaxis, laryngismus, lung disorder, pharyngitis, rhinitis, and sinusitis.

Skin and Appendages: herpes simplex, rash, sweating, and urticaria.

Special Senses: amblyopia.

Urogenital: urinary tract infection.

6.2 Postmarketing Experience

The following adverse reactions have been identified during post approval use of oxycodone. Because these reactions are reported voluntarily from a population of uncertain size, it is not always possible to reliably estimate their frequency or establish a causal relationship to drug exposure. These events include:

Serotonin syndrome: Cases of serotonin syndrome, a potentially life-threatening condition, have been reported during concomitant use of opioids with serotonergic drugs.

Adrenal insufficiency: Cases of adrenal insufficiency have been reported with opioid use, more often following greater than one month of use.

Anaphylaxis: Anaphylaxis has been reported with ingredients contained in OXAYDO.

Androgen deficiency: Cases of androgen deficiency have occurred with use of opioids for an extended period of time [see Clinical Pharmacology (12.2)].

Hyperalgesia and Allodynia: Cases of hyperalgesia and allodynia have been reported with opioid therapy of any duration [see Warnings and Precautions (5.7)]

Hypoglycemia: Cases of hypoglymia have been reported in patients taking opioids. Most reports were in patients with at least one predisposing risk factor (e.g., diabetes).

Opioid-induced esophageal dysfunction (OIED): Cases of OIED have been reported in patients taking opioids, and may occur more frequently in patients taking higher doses of opioids, and/or in patients taking opioids longer term [see Warnings and Precautions (5.12)].

Adverse Reactions from Observational Studies

A prospective, observational cohort study estimated the risks of addiction, abuse, and misuse in patients initiating long-term use of Schedule II opioid analgesics between 2017 and 2021. Study participants included in one or more analyses had been enrolled in selected insurance plans or health systems for at least one year, were free of at least one outcome at baseline, completed a minimum number of follow-up assessments, and either: 1) filled multiple extended-release/long-acting opioid analgesic prescriptions during a 90-day period (n=978); or 2) filled any Schedule II opioid analgesic prescriptions covering at least 70 of 90 days (n=1,244). Those included also had no dispensing of the qualifying opioids in the previous 6 months.

Over 12 months:

- approximately 1% to 6% of participants across the two cohorts newly met criteria for addiction, as assessed with two validated interview-based measures of moderate-to-severe opioid use disorder based on Diagnostic and Statistical Manual of Mental Disorders, Fifth Edition (DSM-5) criteria, and
- approximately 9% and 22% of participants across the two cohorts newly met criteria for prescription opioid abuse and misuse [defined in Drug Abuse and Dependence (9.2)], respectively, as measured with a validated self-reported instrument.

A retrospective, observational cohort study estimated the risk of opioid-involved overdose or opioid overdose-related death in patients with new long-term use of Schedule II opioid analgesics from 2006 through 2016 (n=220,249). Included patients had been enrolled in either one of two commercial insurance programs, one managed care program, or one Medicaid program for at least 9 months. New long-term use was defined as having Schedule II opioid analgesic prescriptions covering at least 70 days’ supply over the 3 months prior to study entry and none during the preceding 6 months. Patients were excluded if they had an opioid-involved overdose in the 9 months prior to study entry. Overdose was measured using a validated medical code-based algorithm with linkage to the National Death Index database. The 5-year cumulative incidence estimates for opioid-involved overdose or opioid overdose-related death ranged from approximately 1.5% to 4% across study sites, counting only the first event during follow-up. Approximately 17% of first opioid overdoses observed over the entire study period (5-11 years, depending on the study site) were fatal. Higher baseline opioid dose was the strongest and most consistent predictor of opioid-involved overdose or opioid overdose-related death. Study exclusion criteria may have selected patients at lower risk of overdose, and substantial loss to follow-up (approximately 80%) also may have biased estimates.

The risk estimates from the studies described above may not be generalizable to all patients receiving opioid analgesics, such as those with exposures shorter or longer than the duration evaluated in the studies.

7 DRUG INTERACTIONS

Table 1 includes clinically significant drug interactions with OXAYDO.

Table 1: Clinically Significant Drug Interactions with OXAYDO
Inhibitors of CYP3A4 and CYP2D6
Clinical Impact: | The concomitant use of OXAYDO and CYP3A4 inhibitors can increase the plasma concentration of oxycodone, resulting in increased or prolonged opioid effects. These effects could be more pronounced with concomitant use of OXAYDO and CYP2D6 and CYP3A4 inhibitors, particularly when an inhibitor is added after a stable dose of OXAYDO is achieved [see Warnings and Precautions (5.6)].; After stopping a CYP3A4 inhibitor, as the effects of the inhibitor decline, the oxycodone plasma concentration will decrease [see Clinical Pharmacology (12.3)], resulting in decreased opioid efficacy or a withdrawal syndrome in patients who had developed physical dependence to oxycodone.
Intervention: | If concomitant use is necessary, consider dosage reduction of OXAYDO until stable drug effects are achieved. Evaluate patients for respiratory depression and sedation at frequent intervals.; If a CYP3A4 inhibitor is discontinued, consider increasing the OXAYDO dosage until stable drug effects are achieved. Evaluate for signs of opioid withdrawal.
Examples | Macrolide antibiotics (e.g., erythromycin), azole-antifungal agents (e.g., ketoconazole), protease inhibitors (e.g., ritonavir)
CYP3A4 Inducers
Clinical Impact: | The concomitant use of OXAYDO and CYP3A4 inducers can decrease the plasma concentration of oxycodone [see Clinical Pharmacology (12.3)], resulting in decreased efficacy or onset of a withdrawal syndrome in patients who have developed physical dependence to oxycodone [see Warnings and Precautions (5.6)].; After stopping a CYP3A4 inducer, as the effects of the inducer decline, the oxycodone plasma concentration will increase [see Clinical Pharmacology (12.3)], which could increase or prolong both the therapeutic effects and adverse reactions, and may cause serious respiratory depression.
Intervention: | If concomitant use is necessary, consider increasing the OXAYDO dosage until stable drug effects are achieved [see Dosage and Administration (2.3)]. Evaluate patients for signs of opioid withdrawal. If a CYP3A4 inducer is discontinued, consider OXAYDO dosage reduction and evaluate patients at frequent intervals for signs of respiratory depression and sedation.
Examples | Rifampin, carbamazepine, phenytoin
Benzodiazepines and other Central Nervous System (CNS) Depressants
Clinical Impact: | Due to additive pharmacologic effect, the concomitant use of benzodiazepines or other CNS depressants including alcohol, increases the risk of respiratory depression, profound sedation, coma, and death [see Warnings and Precautions (5.3)].
Intervention: | Reserve concomitant prescribing of these drugs for use in patients for whom alternative treatment options are inadequate. Limit dosages and durations to the minimum required. Inform patients and caregivers of this potential interaction and educate them on the for signs and symptoms of respiratory depression (including sedation). If concomitant use is warranted, consider recommending or prescribing an opioid overdose reversal agent [see Dosage and Administration (2.2), Warnings and Precautions (5.1, 5.2, 5.3)].
Examples: | Benzodiazepines and other sedatives/hypnotics, anxiolytics, tranquilizers, muscle relaxants, general anesthetics, antipsychotics, gabapentinoids (gabapentin or pregabalin), other opioids, alcohol.
Serotonergic Drugs
Clinical Impact: | The concomitant use of opioids with other drugs that affect the serotonergic neurotransmitter system has resulted in serotonin syndrome.
Intervention: | If concomitant use is warranted, frequently evaluate the patient, particularly during treatment initiation and dose adjustment. Discontinue OXAYDO if serotonin syndrome is suspected.
Examples: | Selective serotonin reuptake inhibitors (SSRIs), serotonin and norepinephrine reuptake inhibitors (SNRIs), tricyclic antidepressants (TCAs), triptans, 5-HT3 receptor antagonists, drugs that affect the serotonin neurotransmitter system (e.g., mirtazapine, trazodone, tramadol), certain muscle relaxants (i.e., cyclobenzaprine, metaxalone), monoamine oxidase (MAO) inhibitors (those intended to treat psychiatric disorders and also others, such as linezolid and intravenous methylene blue).
Monoamine Oxidase Inhibitors (MAOIs)
Clinical Impact: | MAOI interactions with opioids may manifest as serotonin syndrome or opioid toxicity (e.g., respiratory depression, coma) [see Warnings and Precautions (5.2)].
Intervention: | The use of OXAYDO is not recommended for patients taking MAOIs or within 14 days of stopping such treatment.; If urgent use of an opioid is necessary, use test doses and frequent titration of small doses to treat pain while closely monitoring blood pressure and signs and symptoms of CNS and respiratory depression.
Examples: | Phenelzine, tranylcypromine, linezolid
Mixed Agonist/Antagonist and Partial Agonist Opioid Analgesics
Clinical Impact: | May reduce the analgesic effect of OXAYDO and/or precipitate withdrawal symptoms.
Intervention: | Avoid concomitant use.
Examples: | Butorphanol, nalbuphine, pentazocine, buprenorphine
Muscle Relaxants
Clinical Impact: | Oxycodone may enhance the neuromuscular blocking action of skeletal muscle relaxants and produce an increased degree of respiratory depression.
Intervention: | Because respiratory depression may be greater than otherwise expected, decrease the dosage of OXAYDO and/or the muscle relaxant as necessary. Due to the risk of respiratory depression with concomitant use of skeletal muscle relaxants and opioids, consider recommending or prescribing an opioid overdose reversal agent [see Dosage and Administration (2.2), Warnings and Precautions (5.2, 5.3)]
Examples: | Cyclobenzaprine, metaxolone
Diuretics
Clinical Impact: | Opioids can reduce the efficacy of diuretics by inducing the release of antidiuretic hormone.
Intervention: | Evaluate patients for signs of diminished diuresis and/or effects on blood pressure and increase the dosage of the diuretic as needed.
Anticholinergic Drugs
Clinical Impact: | The concomitant use of anticholinergic drugs may increase risk of urinary retention and/or severe constipation, which may lead to paralytic ileus.
Intervention: | Evaluate patients for signs of urinary retention or reduced gastric motility when OXAYDO is used concomitantly with anticholinergic drugs.

8 USE IN SPECIFIC POPULATIONS

8.1 Pregnancy

Risk Summary

Use of opioid analgesics for an extended period of time during pregnancy may cause neonatal opioid withdrawal syndrome [see Warnings and Precautions (5.4)]. There are no available data with OXAYDO in pregnant women to inform a drug-associated risk for major birth defects and miscarriage.

In animal reproduction studies with oral administrations of oxycodone HCl in rats and rabbits during the period of organogenesis at doses 2.6 and 8.1 times, respectively, the human dose of 60 mg/day did not reveal evidence of teratogenicity or embryo-fetal toxicity. In several published studies, treatment of pregnant rats with oxycodone at clinically relevant doses and below resulted in neurobehavioral effects in offspring [see Data]. Based on animal data, advise pregnant women of the potential risk to a fetus.

The background risk of major birth defects and miscarriage for the indicated population is unknown. All pregnancies have a background risk of birth defect, loss, or other adverse outcomes. In the U.S. general population, the estimated background risk of major birth defects and miscarriage in clinically recognized pregnancies is 2 to 4% and 15 to 20%, respectively.

Clinical Considerations

Fetal/Neonatal Adverse Reactions

Use of opioid analgesics for an extended period of time during pregnancy for medical or nonmedical purposes can result in physical dependence in the neonate and neonatal opioid withdrawal syndrome shortly after birth.

Neonatal opioid withdrawal syndrome presents as irritability, hyperactivity and abnormal sleep pattern, high pitched cry, tremor, vomiting, diarrhea, and failure to gain weight. The onset, duration, and severity of neonatal opioid withdrawal syndrome vary based on the specific opioid used, duration of use, timing and amount of last maternal use, and rate of elimination of the drug by the newborn.

Observe newborns for symptoms of neonatal opioid withdrawal syndrome and manage accordingly [see Warnings and Precautions (5.4)].

Labor or Delivery

Opioids cross the placenta and may produce respiratory depression and psycho-physiologic effects in neonates. An opioid overdose reversal agent, such as naloxone or nalmefene, must be available for reversal of opioid-induced respiratory depression in the neonate. OXAYDO is not recommended for use in pregnant women during or immediately prior to labor, when other analgesic techniques are more appropriate. Opioid analgesics, including OXAYDO, can prolong labor through actions which temporarily reduce the strength, duration, and frequency of uterine contractions. However, this effect is not consistent and may be offset by an increased rate of cervical dilation, which tends to shorten labor. Monitor neonates exposed to opioid analgesics during labor for signs of excess sedation and respiratory depression.

Data

Animal Data

In embryo-fetal development studies in rats and rabbits, pregnant animals received oral doses of oxycodone HCl administered during the period of organogenesis up to 16 mg/kg/day and up 25 mg/kg/day, respectively. These studies revealed no evidence of teratogenicity or embryo-fetal toxicity due to oxycodone. The highest doses tested in rats and rabbits were equivalent to approximately 2.6 and 8.1 times an adult human dose of 60 mg/day, respectively, on a mg/m^2 basis. In published studies, offspring of pregnant rats administered oxycodone during gestation have been reported to exhibit neurobehavioral effects including altered stress responses, increased anxiety-like behavior (2 mg/kg/day IV from Gestation Day 8 to 21 and Postnatal Day 1, 3, and 5; 0.3-times an adult human dose of 60 mg/day, on a mg/m^2 basis) and altered learning and memory (15 mg/kg/day orally from breeding through parturition; 2.4 times an adult human dose of 60 mg/day, on a mg/m^2 basis).

8.2 Lactation

Risk Summary

Available data from lactation studies indicate that oxycodone is present in breastmilk and that doses of less than 60 mg/day of the immediate-release formulation are unlikely to result in clinically relevant exposures in breastfed infants. A pharmacokinetics study utilizing opportunistic sampling of 76 lactating women receiving oxycodone immediate-release products for postpartum pain management showed that oxycodone concentrates in breastmilk with an average milk to plasma ratio of 3.2. The relative infant dose was low, approximately 1.3% of a weight-adjusted maternal dose (see Data).

In the same study, among the 70 infants exposed to oxycodone in breastmilk, no adverse events were attributed to oxycodone. However, based on known adverse effects in adults, infants should be monitored for signs of excess sedation and respiratory depression (see Clinical Considerations). There are no data on the effects of the oxycodone on milk production.

The developmental and health benefits of breastfeeding should be considered along with the mother’s clinical need for OXAYDO and any potential adverse effects on the breastfed infant from OXAYDO or from the underlying maternal condition.

Clinical Considerations

Monitor infants exposed to OXAYDO through breast milk for excess sedation and respiratory depression. Withdrawal symptoms can occur in breastfed infants when maternal administration of an opioid analgesic is stopped or when breastfeeding is stopped.

Data

Oxycodone concentration data from 76 lactating women receiving immediate-release oxycodone products for postpartum pain management, and 28 infants exposed to oxycodone in breastmilk showed that following a median (range) dose of oxycodone in mothers of 9.2 (5-10) mg/dose or 33.0 (5.4-59.3) mg/day, oxycodone concentrated in breastmilk with a median (range) milk to plasma ratio of 3.2 (1.2-5.3). However, when using maternal breastmilk data to estimate the daily and relative infant dose, the infant dose was 0.006 mg/kg/day, which is 1.3% of a weight-adjusted maternal dose of 10 mg every 6 hours. These estimates based on maternal breastmilk concentrations were corroborated by the observed infant concentrations, of which over 75% (19/25) were below the limit of quantification. Among the 6 infants with quantifiable concentration, the median (range) concentration was 0.2 ng/mL (0.1-0.7). These concentrations are 100 to 1000 times lower than concentrations observed in other studies after infants received oxycodone at 0.1 mg/kg/dose (~20-200 ng/mL).

8.3 Females and Males of Reproductive Potential

Infertility

Use of opioids for an extended period of time may cause reduced fertility in females and males of reproductive potential. It is not known whether these effects on fertility are reversible [see Adverse Reactions (6.2)].

8.4 Pediatric Use

The safety, effectiveness, and pharmacokinetics of OXAYDO in pediatric patients below the age of 18 have not been established.

8.5 Geriatric Use

Elderly patients (aged 65 years or older) may have increased sensitivity to oxycodone. In general, use caution when selecting a dosage for an elderly patient, usually starting at the low end of the dosing range, reflecting the greater frequency of decreased hepatic, renal, or cardiac function and of concomitant disease or other drug therapy.

Respiratory depression is the chief risk for elderly patients treated with opioids and has occurred after large initial doses were administered to patients who were not opioid-tolerant or when opioids were co-administered with other agents that depress respiration. Titrate the dosage of OXAYDO slowly in geriatric patients frequently reevaluate the patient for signs of central nervous system and respiratory depression [see Warnings and Precautions (5.2)].

Oxycodone is known to be substantially excreted by the kidney, and the risk of adverse reactions to this drug may be greater in patients with impaired renal function. Because elderly patients are more likely to have decreased renal function, care should be taken in dose selection, and it may be useful to regularly evaluate renal function.

8.6 Hepatic Impairment

Since oxycodone is extensively metabolized in the liver, its clearance may decrease in patients with hepatic impairment. Follow a conservative approach to initiate dosing in patients with hepatic impairment. Regularly evaluate patients and adjust the dose based on clinical response [see Dosage and Administration (2.2)].

8.7 Renal Impairment

Information from oxycodone HCl indicates that patients with renal impairment had higher plasma concentrations of oxycodone than subjects with normal renal function. Use a conservative approach to initiate dosing in patients with renal impairment. Regularly evaluate patients and adjust the dose based on clinical response [see Dosage and Administration (2.2)].

9 DRUG ABUSE AND DEPENDENCE

9.1 Controlled Substance

OXAYDO contains oxycodone, a Schedule II controlled substance.

9.2 Abuse

OXAYDO contains oxycodone, a substance with high potential for misuse and abuse, which can lead to the development of substance use disorder, including addiction [see Warnings and Precautions (5.1)].

Misuse is the intentional use, for therapeutic purposes, of a drug by an individual in a way other than prescribed by a healthcare provider or for whom it was not prescribed.

Abuse is the intentional, non-therapeutic use of a drug, even once, for its desirable psychological or physiological effects.

Drug addiction is a cluster of behavioral, cognitive, and physiological phenomena that may include a strong desire to take the drug, difficulties in controlling drug use (e.g., continuing drug use despite harmful consequences, giving a higher priority to drug use than other activities and obligations), and possible tolerance or physical dependence.

Misuse and abuse of OXAYDO increases risk of overdose, which may lead to central nervous system and respiratory depression, hypotension, seizures, and death. The risk is increased with concurrent abuse of OXAYDO with alcohol and/or other CNS depressants. Abuse of and addiction to opioids in some individuals may not be accompanied by concurrent tolerance and symptoms of physical dependence. In addition, abuse of opioids can occur in the absence of addiction.

All patients treated with opioids require careful and frequent reevaluation for signs of misuse, abuse, and addiction, because use of opioid analgesic products carries the risk of addiction even under appropriate medical use. Patients at high risk of OXAYDO abuse include those with a history of prolonged use of any opioid, including products containing oxycodone, those with a history of drug or alcohol abuse, or those who use OXAYDO in combination with other abused drugs.

“Drug-seeking” behavior is very common in persons with substance use disorders. Drug-seeking tactics include emergency calls or visits near the end of office hours, refusal to undergo appropriate examination, testing, or referral, repeated “loss” of prescriptions, tampering with prescriptions, and reluctance to provide prior medical records or contact information for other treating healthcare provider(s). “Doctor shopping” (visiting multiple prescribers to obtain additional prescriptions) is common among people who abuse drugs and people with substance use disorder. Preoccupation with achieving adequate pain relief can be appropriate behavior in a patient with inadequate pain control.

OXAYDO, like other opioids, can be diverted for nonmedical use into illicit channels of distribution. Careful record-keeping of prescribing information, including quantity, frequency, and renewal requests, as required by state and federal law, is strongly advised.

Proper assessment of the patient, proper prescribing practices, periodic reevaluation of therapy, and proper dispensing and storage are appropriate measures that help to limit abuse of opioid drugs.

Risks Specific to Abuse of OXAYDO

Abuse of OXAYDO poses a risk of overdose and death. The risk is increased with concurrent use of OXAYDO with alcohol and/or other CNS depressants.

OXAYDO is intended for oral use only.

Parenteral drug abuse is commonly associated with transmission of infectious diseases such as hepatitis and HIV.

In a double-blind, active-comparator, crossover study in 40 non-dependent recreational opioid users, “drug liking” responses and single-dose safety of crushed OXAYDO tablets were compared with crushed immediate-release oxycodone tablets when subjects self-administered the drug intranasally. The presence of sequence effects resulted in questionable reliability of the second period data. First period data demonstrated small numeric differences in the median and mean drug liking scores, lower in response to OXAYDO than immediate-release oxycodone. Thirty percent of subjects exposed to OXAYDO responded that they would not take the drug again compared to 5% of subjects exposed to immediate-release oxycodone. Study subjects self-administering OXAYDO reported a higher incidence of nasopharyngeal and facial adverse events and a decreased ability to completely insufflate two crushed tablets within a fixed time period (21 of 40 subjects). The clinical significance of the difference in drug liking and difference in response to taking the drug again reported in this study has not yet been established. There is no evidence that OXAYDO has a reduced abuse liability compared to immediate-release oxycodone.

9.3 Dependence

Both tolerance and physical dependence can develop during use of opioid therapy.

Tolerance is a physiological state characterized by a reduced response to a drug after repeated administration (i.e., a higher dose of a drug is required to produce the same effect that was once obtained at a lower dose).

Physical dependence is a state that develops as a result of a physiological adaptation in response to repeated drug use, manifested by withdrawal signs and symptoms after abrupt discontinuation or a significant dose reduction of a drug.

Withdrawal may be precipitated through the administration of drugs with opioid antagonist activity (e.g., naloxone or nalmefene), mixed agonist/antagonist analgesics (e.g., pentazocine, butorphanol, nalbuphine), or partial agonists (e.g., buprenorphine). Physical dependence may not occur to a clinically significant degree until after several days to weeks of continued use.

Do not rapidly reduce or abruptly discontinue OXAYDO in a patient physically dependent on opioids. Rapid tapering of OXAYDO in a patient physically dependent on opioids may lead to serious withdrawal symptoms, uncontrolled pain, and suicide. Rapid discontinuation has also been associated with attempts to find other sources of opioid analgesics, which may be confused with drug-seeking for abuse.

When discontinuing OXAYDO, gradually taper the dosage using a patient-specific plan that considers the following: the dose of OXAYDO the patient has been taking, the duration of treatment, and the physical and psychological attributes of the patient. To improve the likelihood of a successful taper and minimize withdrawal symptoms, it is important that the opioid tapering schedule is agreed upon by the patient. In patients taking opioids for an extended period of time at high doses, ensure that a multimodal approach to pain management, including mental health support (if needed), is in place prior to initiating an opioid analgesic taper [see Dosage and Administration (2.5), and Warnings and Precautions (5.14)].

Infants born to mothers physically dependent on opioids will also be physically dependent and may exhibit respiratory difficulties and withdrawal signs [see Use in Specific Populations (8.1)].

10 OVERDOSAGE

Clinical Presentation

Acute overdose with oxycodone can be manifested by respiratory depression, somnolence progressing to stupor or coma, skeletal muscle flaccidity, cold and clammy skin, constricted pupils, and, in some cases, pulmonary edema, bradycardia, hypotension, hypoglycemia, partial or complete airway obstruction, atypical snoring, and death. Marked mydriasis rather than miosis may be seen with hypoxia in overdose situations [see Clinical Pharmacology (12.2)]. Toxic leukoencephalopathy has been reported after opioid overdose and can present hours, days, or weeks after apparent recovery from the initial intoxication.

Treatment of Overdose

In case of overdose, priorities are the reestablishment of a patent and protected airway and institution of assisted or controlled ventilation, if needed. Employ other supportive measures (including oxygen and vasopressors) in the management of circulatory shock and pulmonary edema as indicated. Cardiac arrest or arrhythmias may require advanced life-support measures.

For clinically significant respiratory or circulatory depression secondary to opioid overdose, administer an opioid overdose reversal agent such as naloxone or nalmefene.

Because the duration of opioid reversal is expected to be less than the duration of action of oxycodone in OXAYDO, carefully monitor the patient until spontaneous respiration is reliably reestablished. If the response to an opioid overdose reversal agent is suboptimal or only brief in nature, administer additional reversal agent as directed by the product’s prescribing information.

In an individual physically dependent on opioids, administration of the recommended usual dosage of the opioid overdose reversal agent will precipitate an acute withdrawal syndrome. The severity of the withdrawal symptoms experienced will depend on the degree of physical dependence and the dose of the reversal agent administered. If a decision is made to treat serious respiratory depression in the physically dependent patient, administration of the reversal agent should be initiated with care and by titration with smaller than usual doses of the reversal agent.

11 DESCRIPTION

OXAYDO (oxycodone HCl) 5 mg and 7.5 mg tablets are an immediate-release opioid agonist intended for oral administration only.

Chemically, oxycodone HCl is 4,5α-epoxy-14-hydroxy-3-methoxy-17-methylmorphinan-6-one HCl, a white, odorless crystalline powder. Oxycodone HCl is soluble in water (1 g in 6 to 7 mL). The molecular weight of oxycodone HCl is 351.82. The molecular formula for oxycodone HCl is C18H21NO4•HCl, and the structure is:

The inactive ingredients in OXAYDO include: colloidal silicon dioxide NF; crospovidone NF; magnesium stearate NF; microcrystalline cellulose NF; polyethylene oxide NF; and sodium lauryl sulfate NF.

The tablets are round, convex, white and debossed with the strength (5 or 7.5) on one side and the letter “O” on the other side.

12 CLINICAL PHARMACOLOGY

12.1 Mechanism of Action

Oxycodone is a full opioid agonist and is relatively selective for the mu-opioid receptor, although it can bind to other opioid receptors at higher doses. The principal therapeutic action of oxycodone is analgesia. Like all full opioid agonists, there is no ceiling effect for analgesia with oxycodone. Clinically, dosage is titrated to provide adequate analgesia and may be limited by adverse reactions, including respiratory and CNS depression.

The precise mechanism of the analgesic action is unknown. However, specific CNS opioid receptors for endogenous compounds with opioid-like activity have been identified throughout the brain and spinal cord and are thought to play a role in the analgesic effects of this drug.

12.2 Pharmacodynamics

Effects on the Central Nervous System

Oxycodone produces respiratory depression by direct action on brainstem respiratory centers. The respiratory depression involves a reduction in the responsiveness of the brain stem respiratory centers to both increases in carbon dioxide tension and electrical stimulation.

Oxycodone causes miosis, even in total darkness. Pinpoint pupils are a sign of opioid overdose but are not pathognomonic (e.g., pontine lesions of hemorrhagic or ischemic origins may produce similar findings). Marked mydriasis rather than miosis may be seen due to hypoxia in overdose situations.

Effects on the Gastrointestinal Tract and Other Smooth Muscle

Oxycodone causes a reduction in motility associated with an increase in smooth muscle tone in the antrum of the stomach and duodenum. Digestion of food in the small intestine is delayed and propulsive contractions are decreased. Propulsive peristaltic waves in the colon are decreased, while tone may be increased to the point of spasm, resulting in constipation. Other opioid-induced effects may include a reduction in biliary and pancreatic secretions, spasm of sphincter of Oddi, transient elevations in serum amylase, and opioid-induced esophageal dysfunction (OIED).

Effects on the Cardiovascular System

Oxycodone produces peripheral vasodilation which may result in orthostatic hypotension or syncope. Manifestations of histamine release and/or peripheral vasodilation may include pruritus, flushing, red eyes and sweating, and/or orthostatic hypotension.

Effects on the Endocrine System

Opioids inhibit the secretion of adrenocorticotropic hormone (ACTH), cortisol, and luteinizing hormone (LH) in humans [see Adverse Reactions (6.2)]. They also stimulate prolactin, growth hormone (GH) secretion, and pancreatic secretion of insulin and glucagon.

Use of opioids for an extended period of time may influence the hypothalamic-pituitary-gonadal axis, leading to androgen deficiency that may manifest as low libido, impotence, erectile dysfunction, amenorrhea, or infertility. The causal role of opioids in the clinical syndrome of hypogonadism is unknown because the various medical, physical, lifestyle, and psychological stressors that may influence gonadal hormone levels have not been adequately controlled for in studies conducted to date [see Adverse Reactions (6.2)].

Effects on the Immune System

Opioids have been shown to have a variety of effects on components of the immune system in in vitro and animal models. The clinical significance of these findings is unknown. Overall, the effects of opioids appear to be modestly immunosuppressive.

Concentration–Efficacy Relationships

The minimum effective analgesic concentration will vary widely among patients, especially among patients who have been previously treated with opioid agonists. The minimum effective analgesic concentration of oxycodone for any individual patient may increase over time due to an increase in pain, the development of a new pain syndrome, and/or the development of analgesic tolerance [see Dosage and Administration (2.1, 2.4)].

Concentration–Adverse Reaction Relationships

There is a relationship between increasing oxycodone plasma concentration and increasing frequency of dose-related opioid adverse reactions such as nausea, vomiting, CNS effects, and respiratory depression. In opioid-tolerant patients, the situation may be altered by the development of tolerance to opioid-related adverse reactions [see Dosage and Administration (2.1, 2.4)].

12.3 Pharmacokinetics

The analgesic activity of OXAYDO is primarily due to the parent drug oxycodone.

The pharmacokinetics of oxycodone after OXAYDO administration are characterized by peak plasma concentrations occurring on average within 1.2 to 1.4 hours of the first dose under fasted conditions. Thereafter, oxycodone concentrations fall with an average terminal half-life ranging between 3-4 hours. OXAYDO is bioequivalent with oxycodone immediate-release tablets in the fasted state, with no differences identified in the time to peak exposure (Tmax) and terminal elimination half-life (T½) of oxycodone between administration of OXAYDO and oxycodone immediate-release tablets. Dose proportionality was established for OXAYDO at doses of 5 mg, 10 mg, and 15 mg (oxycodone HCl) based on proportional increases in oxycodone Cmax and AUC exposure levels.

Absorption

The oral bioavailability of oxycodone is 60% to 87%. The high oral bioavailability of oxycodone (compared to other oral opioids) is due to lower pre-systemic and/or first-pass metabolism of oxycodone compared to other oral opioids.

Food Effect

When administered with a high fat meal, mean AUC values are increased by 21% and peak concentrations are decreased by 14%. Food causes a delay in Tmax from 1.25 to 3.00 hours. These changes in oxycodone pharmacokinetics are not considered clinically relevant; therefore, OXAYDO can be taken without regard to food.

Distribution

Following intravenous administration, the volume of distribution for oxycodone was 2.6 L/kg. Plasma protein binding of oxycodone at 37°C and a pH of 7.4 was approximately 45%. Oxycodone has been found in breast milk [see Use in Specific Populations (8.2)].

Elimination

The total plasma clearance of oxycodone is 0.8 L/min for adults. Apparent elimination half-life of oxycodone following the administration of oxycodone was 3.5 to 4 hours.

Metabolism

Oxycodone HCl is extensively metabolized by multiple metabolic pathways to noroxycodone, oxymorphone, and noroxymorphone, which are subsequently glucuronidated. CYP3A4 mediated N-demethylation to noroxycodone is the primary metabolic pathway of oxycodone with less contribution from CYP2D6 mediated O-demethylation to oxymorphone. Therefore, the formation of these and related metabolites can, in theory, be affected by other drugs. The major circulating metabolite is noroxycodone with an AUC ratio of 0.6 relative to that of oxycodone. Noroxycodone is reported to be a considerably weaker analgesic than oxycodone. Oxymorphone, although possessing analgesic activity, is present in the plasma only in low concentrations. The correlation between oxymorphone concentrations and opioid effects was much less than that seen with oxycodone plasma concentrations. The analgesic activity profile of other metabolites is not known.

Excretion

Oxycodone and its metabolites are excreted primarily via the kidney. The amounts measured in the urine have been reported as follows: free oxycodone up to 19%; conjugated oxycodone up to 50%; free oxymorphone 0%; and conjugated oxymorphone ≤14%. Both free and conjugated noroxycodone have been found in urine but not quantified.

Specific Populations

Age: Geriatric Population

Information obtained for oxycodone indicates that the plasma concentrations of oxycodone did not appear to be increased in patients over the age of 65.

Sex

Information obtained for oxycodone support the lack of sex effect on the pharmacokinetics of oxycodone.

Renal Impairment

Information obtained for oxycodone indicates that patients with renal impairment had higher plasma concentrations of oxycodone than subjects with normal renal function [see Use in Specific Populations (8.7)].

Hepatic Impairment

Since oxycodone is extensively metabolized in the liver, its clearance may decrease in patients with hepatic impairment [see Use in Specific Populations (8.6)].

Drug Interaction Studies

CYP3A4 Inhibitors

CYP3A4 is the major enzyme involved in noroxycodone formation. A published study showed that the coadministration of voriconazole, a CYP3A4 inhibitor, increased oxycodone AUC and Cmax by 3.6 and 1.7 fold, respectively [see Warnings and Precautions (5.6) and Drug Interactions (7)].

CYP3A4 Inducers

A published study showed that the co-administration of rifampin, a drug metabolizing enzyme inducer, decreased oxycodone AUC and Cmax values by 86% and 63%, respectively [see Warnings and Precautions (5.6) and Drug Interactions (7)].

CYP2D6 Inhibitors

Oxycodone is metabolized in part to oxymorphone via the cytochrome p450 isoenzyme CYP2D6. While this pathway may be blocked by a variety of drugs (e.g., certain cardiovascular drugs and antidepressants), such blockade has not yet been shown to be of clinical significance with OXAYDO.

13 NONCLINICAL TOXICOLOGY

13.1 Carcinogenesis, Mutagenesis, Impairment of Fertility

Carcinogenesis

Long-term studies in animals to evaluate its carcinogenic potential of oxycodone have not been conducted.

Mutagenesis

Oxycodone was genotoxic in an in vitro mouse lymphoma assay in the presence of metabolic activation. There was no evidence of genotoxic potential in an in vitro bacterial reverse mutation assay (Salmonella typhimurium and Escherichia coli) and in an assay for chromosomal aberrations (in vivo mouse bone marrow micronucleus assay).

Impairment of Fertility

Studies in animals to evaluate the potential impact of oxycodone on fertility have not been conducted.

16 HOW SUPPLIED/STORAGE AND HANDLING

OXAYDO (oxycodone HCl) 5 mg tablets are round, convex, white tablets debossed with the strength “5” on one side and the letter “O” on the other side and supplied as:

NDC 69344-113-11 Bottles of 100 tablets

OXAYDO 7.5 mg tablets are round, convex, white tablets debossed with the strength “7.5” on one side and the letter “O” on the other side and supplied as:

NDC 69344-213-11 Bottles of 100 tablets

Dispense in tight container as defined in the USP, with a child-resistant closure.

Store at 25°C (77°F); with excursions permitted to 15°-30°C (59°-86°F) [See USP Controlled Room Temperature].

Protect from moisture.

Store OXAYDO securely and dispose of properly.

17 PATIENT COUNSELING INFORMATION

Advise the patient to read the FDA-approved patient labeling (Medication Guide).

Storage and Disposal:

Because of the risks associated with accidental ingestion, misuse, and abuse, advise patients to store OXAYDO securely, out of sight and reach of children, and in a location not accessible by others, including visitors to the home. Inform patients that leaving OXAYDO unsecured can pose a deadly risk to others in the home [see Warnings and Precautions (5.1, 5.2), Drug Abuse and Dependence (9.2)].

Advise patients and caregivers that when medicines are no longer needed, they should be disposed of promptly. Expired, unwanted, or unused OXAYDO should be disposed of by flushing the unused medication down the toilet if a drug take-back option is not readily available. Inform patients that they can visit www.fda.gov/drugdisposal for a complete list of medicines recommended for disposal by flushing, as well as additional information on disposal of unused medicines.

Addiction, Abuse, and Misuse

Inform patients that the use of OXAYDO, even when taken as recommended, can result in addiction, abuse, and misuse, which can lead to overdose and death [see Warnings and Precautions (5.1)]. Instruct patients not to share OXAYDO with others and to take steps to protect OXAYDO from theft or misuse.

Life-Threatening Respiratory Depression

Inform patients of the risk of life-threatening respiratory depression, including information that the risk is greatest when starting OXAYDO or when the dosage is increased, and that it can occur even at recommended dosages. Educate patients and caregivers on how to recognize respiratory depression and emphasize the importance of calling 911 or getting emergency medical help right away in the event of a known or suspected overdose [see Warnings and Precautions (5.2)].

Accidental Ingestion

Inform patients that accidental ingestion, especially by children, may result in respiratory depression or death [see Warnings and Precautions (5.2)].

Interactions with Benzodiazepines and Other CNS Depressants

Inform patients and caregivers that potentially fatal additive effects may occur if OXAYDO is used with benzodiazepines or other CNS depressants, including alcohol (e.g., non-benzodiazepine sedative/hypnotics, anxiolytics, tranquilizers, muscle relaxants, general anesthetics, antipsychotics, gabapentinoids [gabapentin or pregabalin], and other opioids), and not to use these concomitantly unless supervised by a healthcare provider [see Warnings and Precautions (5.3), Drug Interactions (7)].

Patient Access to an Opioid Overdose Reversal Agent for the Emergency Treatment of Opioid Overdose

Inform patients and caregivers about opioid overdose reversal agents (e.g., naloxone, nalmefene). Discuss the importance of having access to an opioid overdose reversal agent, especially if the patient has risk factors for overdose (e.g., concomitant use of CNS depressants, a history of opioid use disorder, or prior opioid overdose) or if there are household members (including children) or other close contacts at risk for accidental ingestion or opioid overdose.

Discuss with the patient the options for obtaining an opioid overdose reversal agent (e.g., prescription, over-the-counter, or as part of a community-based program) [see Dosage and Administration (2.2), Warnings and Precautions (5.3)].

Educate patients and caregivers on how to recognize the signs and symptoms of an overdose.

Explain to patients and caregivers that effects of opioid overdose reversal agents like naloxone and nalmefene are temporary and that they must call 911 or get emergency medical help right away in all cases of known or suspected opioid overdose, even if an opioid overdose reversal agent is administered [see Overdosage (10)].

Advise patients and caregivers:

- how to treat with the overdose reversal agent in the event of an opioid overdose

- to tell family and friends about their opioid overdose reversal agent, and to keep it in a place where family and friends can access it in an emergency

- to read the Patient Information (or other education material) that will come with their opioid overdose reversal agent. Emphasize the importance of doing this before an opioid emergency happens, so the patient and caregiver will know what to do.

Hyperalgesia and Allodynia

Inform patients and caregivers not to increase opioid dosage without first consulting a clinician. Advise patients to seek medical attention if they experience symptoms of hyperalgesia, including worsening pain, increased sensitivity to pain, or new pain [see Warnings and Precautions (5.7), Adverse Reaction (6.2)].

Serotonin Syndrome

Inform patients that opioids could cause a rare but potentially life-threatening condition called serotonin syndrome resulting from concomitant administration of serotonergic drugs. Warn patients of the symptoms of serotonin syndrome and to seek medical attention right away if symptoms develop. Instruct patients to inform their healthcare providers if they are taking, or plan to take serotonergic medications. [see Drug Interactions (7)].

MAOI Interaction

Inform patients to avoid taking OXAYDO while using any drugs that inhibit monoamine oxidase. Patients should not start MAOIs while taking OXAYDO [see Drug Interactions (7)].

Important Administration Instructions

Instruct patients how to properly take OXAYDO [see Dosage and Administration (2), Warnings and Precautions (5)]. Advise patients:

- that OXAYDO is a narcotic pain reliever and must be taken only as directed.
- not to pre-soak, lick or otherwise wet the tablet prior to placing in the mouth.
- to take each tablet with enough water to ensure complete swallowing immediately after placing in the mouth.
- that OXAYDO tablets must be swallowed whole and not crushed or dissolved.
- that OXAYDO is not for administration via nasogastric, gastric or other feeding tubes as it may cause obstruction of feeding tubes.
- that if they miss a dose to take it as soon as possible. If it is almost time for the next dose, advise to skip the missed dose and take the next dose at the regularly scheduled time. Advise patients not to take 2 doses at once unless instructed by their healthcare provider. If they are not sure about their dosing, call their healthcare provider.
- not to adjust the dose of OXAYDO without consulting with a physician or other healthcare professional.

Important Discontinuation Instructions

In order to avoid developing withdrawal symptoms, instruct patients not to discontinue OXAYDO without first discussing a tapering plan with the prescriber [see Dosage and Administration (2.5)].

Driving or Operating Heavy Machinery

Inform patients that OXAYDO may impair the ability to perform potentially hazardous activities such as driving a car or operating heavy machinery. Advise patients not to perform such tasks until they know how they will react to the medication [see Warnings and Precautions (5.15)].

Constipation

Advise patients of the potential for severe constipation, including management instructions and when to seek medical attention [see Adverse Reactions (6), Clinical Pharmacology (12.2)].

Adrenal Insufficiency

Inform patients that opioids could cause adrenal insufficiency, a potentially life-threatening condition. Adrenal insufficiency may present with non-specific symptoms and signs such as nausea, vomiting, anorexia, fatigue, weakness, dizziness, and low blood pressure. Advise patients to seek medical attention if they experience a constellation of these symptoms [see Warnings and Precautions (5.9)].

Hypotension

Inform patients that OXAYDO may cause orthostatic hypotension and syncope. Instruct patients how to recognize symptoms of low blood pressure and how to reduce the risk of serious consequences should hypotension occur (e.g., sit or lie down, carefully rise from a sitting or lying position) [see Warnings and Precautions (5.10)].

Anaphylaxis

Inform patients that anaphylaxis has been reported with ingredients contained in OXAYDO. Advise patients how to recognize such a reaction and when to seek medical attention [see Contraindications (4), Adverse Reactions (6)].

Pregnancy

Neonatal Opioid Withdrawal Syndrome

Inform female patients of reproductive potential that use of OXAYDO for an extended period of time during pregnancy can result in neonatal opioid withdrawal syndrome, which may be life-threatening if not recognized and treated [see Warnings and Precautions (5.4), Use in Specific Populations (8.1)].

Embryo-Fetal Toxicity

Inform female patients of reproductive potential that OXAYDO can cause fetal harm and to inform the healthcare provider of a known or suspected pregnancy [see Use in Specific Populations (8.1)].

Lactation

Advise breastfeeding women using OXAYDO to carefully observe infants for increased sleepiness (more than usual), breathing difficulties, or limpness. Instruct breastfeeding women to seek immediate medical care if they notice these signs [see Use in Specific Populations (8.2)].

Infertility

Inform patients that use of opioids for an extended period of time may cause reduced fertility. It is not known whether these effects on fertility are reversible [see Use in Specific Populations (8.3)].

Distributed by:

Zyla Life Sciences US LLC
Lake Forest, IL

60045

© 2020 Zyla Life Sciences. All rights reserved.

12/2025
LBL #: 201.09

Medication Guide

OXAYDO (ox Ā doe)
(oxycodone HCl, USP) Tablets for oral use only, CII

OXAYDO is:

- A strong prescription pain medicine that contains an opioid (narcotic) that is used to manage short-term (acute) and long term (chronic) pain severe enough to require an opioid pain medicine, when other pain treatments such as non-opioid pain medicines do not treat your pain well enough or you cannot tolerate them.
- An opioid pain medicine that can put you at risk for overdose and death. Even if you take your dose correctly as prescribed you are at risk for opioid addiction, abuse, and misuse that can lead to death.

Important information about OXAYDO:

- Get emergency help right away or call 911 right away if you take too much OXAYDO (overdose). When you first start taking OXAYDO, when your dose is changed, or if you take too much (overdose), serious or life-threatening breathing problems that can lead to death may occur. Ask your healthcare provider about medicines like naloxone or nalmefene that can be used in an emergency to reverse an opioid overdose.
- Taking OXAYDO with other opioid medicines, benzodiazepines, gabapentinoids (gabapentin or pregabalin), alcohol, or other central nervous system depressants (including street drugs) can cause severe drowsiness, decreased awareness, breathing problems, coma, and death.
- Never give anyone else your OXAYDO. They could die from taking it. Selling or giving away OXAYDO is against the law.
- Store OXAYDO securely, out of sight and reach of children, and in a location not accessible by others, including visitors to the home.

Do not take OXAYDO if you have:

- severe asthma, trouble breathing, or other lung problems.
- a bowel blockage or have narrowing of the stomach or intestines.

Before taking OXAYDO, tell your healthcare provider if you have a history of:

- head injury, seizures
- problems urinating
- abuse of street or prescription drugs, alcohol addiction, opioid overdose, or mental health problems.

- liver, kidney, thyroid problems
- pancreas or gallbladder problems

Tell your healthcare provider if you are:

- noticing your pain getting worse. If your pain gets worse after you take OXAYDO, do not take more of OXAYDO without first talking to your healthcare provider. Talk to your healthcare provider if the pain that you have increases, if you feel more sensitive to pain, or if you have new pain after taking OXAYDO.
- pregnant or planning to become pregnant. Use of OXAYDO for an extended period of time during pregnancy can cause withdrawal symptoms in your newborn baby that could be life-threatening if not recognized and treated.
- breastfeeding. OXAYDO passes into breastmilk and may harm your baby. Carefully observe infants for increased sleepiness (more than usual), breathing difficulties, or limpness. Seek immediate medical care if you notice these signs.
- living in a household where there are small children or someone who has abused street or prescription drugs.
- taking prescription or over-the-counter medicines, vitamins, or herbal supplements. Taking OXAYDO with certain other medicines can cause serious side effects that could lead to death.

When taking OXAYDO:

- Do not change your dose. Take OXAYDO exactly as prescribed by your healthcare provider. Use the lowest dose possible for the shortest time needed.
- For acute (short-term) pain, you may only need to take OXAYDO for a few days. You may have some OXAYDO left over that you did not use. See disposal information at the bottom of this section for directions on how to safely throw away (dispose of) your unused OXAYDO.
- Take your prescribed dose exactly as instructed by your healthcare provider. Your healthcare provider may adjust the dose until it is right for you. Do not take more than your prescribed dose. If you miss a dose, take your next dose at your usual time.
- Call your healthcare provider if the dose you are taking does not control your pain.
- If you have been taking OXAYDO regularly, do not stop taking OXAYDO without talking to your healthcare provider.
- Dispose of expired, unwanted, or unused OXAYDO by promptly flushing down the toilet, if a drug take-back option is not readily available. Visit www.fda.gov/drugdisposal for additional information on disposal of unused medicines.

While taking OXAYDO DO NOT:

- Drive or operate heavy machinery, until you know how OXAYDO affects you. OXAYDO can make you sleepy, dizzy, or lightheaded.
- Drink alcohol or use prescription or over-the-counter medicines that contain alcohol. Using products containing alcohol during treatment with OXAYDO may cause you to overdose and die.

The possible side effects of OXAYDO:

- constipation, nausea, sleepiness, vomiting, tiredness, headache, dizziness, abdominal pain. Call your healthcare provider if you have any of these symptoms and they are severe.

Get emergency medical help or call 911 right away if you have:

- trouble breathing, shortness of breath, fast heartbeat, chest pain, swelling of your face, tongue, or throat, extreme drowsiness, light-headedness when changing positions, feeling faint, agitation, high body temperature, trouble walking, stiff muscles, or mental changes such as confusion.

These are not all the possible side effects of OXAYDO. Call your healthcare provider for medical advice about side effects. You may report side effects to FDA at 1-800-FDA-1088. For more information go to dailymed.nlm.nih.gov

Distributed by: Zyla Life Sciences US Inc., Wayne, PA, 19087; for more information go to www.oxaydo.com or call 1-800-518-1084

This Medication Guide has been approved by the U.S. Food and Drug Administration.

Issued: 12/2025